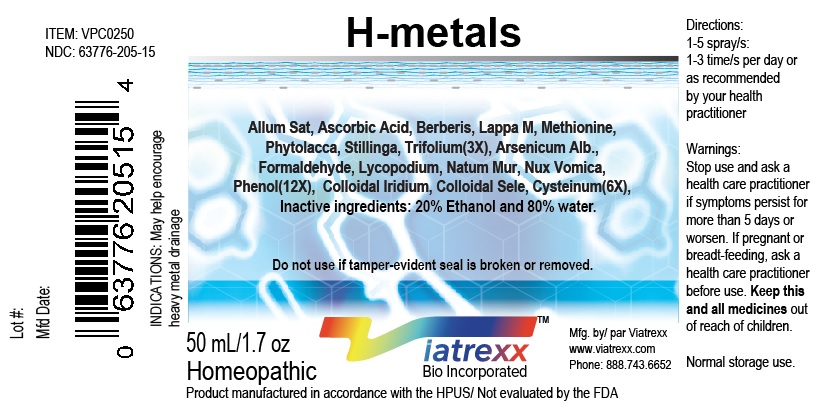 DRUG LABEL: Viatrexx-H Metals
NDC: 63776-205 | Form: SPRAY
Manufacturer: VIATREXX BIO INCORPORATED
Category: homeopathic | Type: HUMAN OTC DRUG LABEL
Date: 20190319

ACTIVE INGREDIENTS: Garlic 3 [hp_X]/1 mL; Arsenic Trioxide 12 [hp_X]/1 mL; Ascorbic Acid 3 [hp_X]/1 mL; Berberis Vulgaris Root Bark 3 [hp_X]/1 mL; Iridium 6 [hp_X]/1 mL; Selenium 6 [hp_X]/1 mL; Cysteine 6 [hp_X]/1 mL; Formaldehyde 12 [hp_X]/1 mL; Arctium Lappa Root 3 [hp_X]/1 mL; Lycopodium Clavatum Spore 12 [hp_X]/1 mL; Methionine 3 [hp_X]/1 mL; Sodium Chloride 12 [hp_X]/1 mL; Strychnos Nux-Vomica Seed 12 [hp_X]/1 mL; Phenol 12 [hp_X]/1 mL; Phytolacca Americana Root 3 [hp_X]/1 mL; Stillingia Sylvatica Root 3 [hp_X]/1 mL; Red Clover 3 [hp_X]/1 mL
INACTIVE INGREDIENTS: Water; Alcohol

H Metals

Active Ingredients

Allum Sativa 3X, Arsenicum Alb 12X, Ascorbic Acid 3X, Berberis 3X, Iridium 6X, Selenium 6X, Cysteinum 6X, Formaldehyde 12X, Lappa M 3X, Lycopodium 12X, Methionine 3X, Natrum Mur 12X, Nux Vomica 12X, Phenol 12X, Phytolacca 3X, Stillinga 3X, Trifolium 3X

Purpose

Allum Sat 3X Drainage
Arsenicum Alb. 12X Drainage
Ascorbic Acid 3X Anti-oxidant
Berberis 3X Urogenital drainage
Iridium 6X Drainage
Selenium 6X Metabolism
Cysteinum 6X Drainage, metabolism
Formaldehyde 12X Drainage
Lappa M 3X Immune support
Lycopodium 12X Drainage
Methionine 3X Drainage
Natum Mur 12X Metabolism
Nux Vomica 12X Drainage
Phenol 12X Drainage
Phytolacca 3X Drainage
Stillinga 3X Regeneration, drainage
Trifolium 3X Drainage, regeneration

Description

Viatrexx-H Metals is a homeopathic product composed of physiological (low dose and low low dose) natural micro nutrients. These micro particles are designed to nourish the system.

Uses

May help encourage heavy metal drainage

Warnings

Stop use and ask a health care practitioner if symptoms persist for more than five days or worsen. If pregnant or breastfeeding, ask a health care practitioner before use.

Dosage

1-3 spray(s); 1-3 time(s) per day or as recommended by your health care practitioner.

Inactive Ingredients

20% Alcohol and 80% Water

Other Information

Product availability

Product may be acquired in 0.5, 30, 50, 100, 250 mL bottles.

References upon request

To report SUSPECTED ADVERSE REACTIONS, contact the FDA at 1-800-FDA-1088 or www.fda.gov/medwatch

Distributed by
Viatrexx Bio Incorporated
Newark, DE, USA, 19713

Manufactured by
8046255 Canada Inc
Beloeil, Qc, J3G 6S3
Date of last revision March 2019

For Questions and comments
Info@Viatrexx.com
www.Viatrexx.com

PACKAGE LABEL.PRINCIPAL DISPLAY PANEL

NDC: 63776-205-11
Item: VPC0250
Viatrexx Bio Incorporated
Viatrexx- H-Metals
Box of 1 X 0.5 mL ampule
For Oral and Topical Use
Expiry date: Lot #:
Manufactured for:
Viatrexx Bio Incorporated Newark, DE, USA, 19713
www.Viatrexx.com
Ingredients, homeopathic
See insert or www.viatrexx.com
Inactives: Alcohol 20%, Water 80%

NDC: 63776-205-14
Item: VPC0250
Viatrexx Bio Incorporated
Viatrexx-H-Metals
Box of 1 X 30 mL spray bottle
For Oral and Topical Use
Expiry date: Lot #:
Manufactured for:
Viatrexx Bio Incorporated Newark, DE, USA, 19713
www.Viatrexx.com
Ingredients, homeopathic
See insert or www.viatrexx.com
Inactives: Alcohol 20%, Water 80%

NDC: 63776-205-15
Item: VPC0250
Viatrexx Bio Incorporated
Viatrexx-H-Metals
Box of 1 X 50 mL spray bottle
For Oral and Topical Use
Expiry date: Lot #:
Manufactured for:
Viatrexx Bio Incorporated Newark, DE, USA, 19713
www.Viatrexx.com
Ingredients, homeopathic
See insert or www.viatrexx.com
Inactives: Alcohol 20%, Water 80%

NDC: 63776-205-16
Item: VPC0250
Viatrexx Bio Incorporated
Viatrexx-H-Metals
Box of 1 X 100 mL bottle
For Oral and Topical Use
Expiry date: Lot #:
Manufactured for:
Viatrexx Bio Incorporated Newark, DE, USA, 19713
www.Viatrexx.com
Ingredients, homeopathic
See insert or www.viatrexx.com
Inactives: Alcohol 20%, Water 80%

NDC: 63776-205-17
Item: VPC0250
Viatrexx Bio Incorporated
Viatrexx-H-Metals
Box of 1 X 250 mL bottle
For Oral and Topical Use
Expiry date: Lot #:
Manufactured for:
Viatrexx Bio Incorporated Newark, DE, USA, 19713
www.Viatrexx.com
Ingredients, homeopathic
See insert or www.viatrexx.com
Inactives: Alcohol 20%, Water 80%